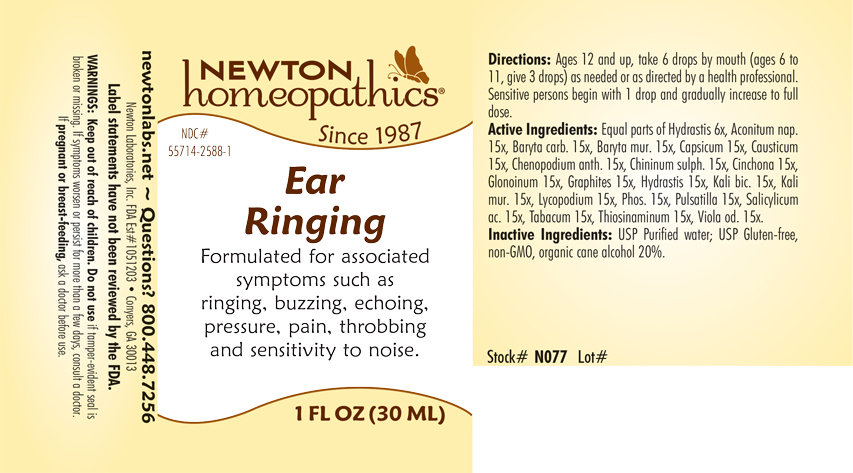 DRUG LABEL: Ear Ringing
NDC: 55714-2588 | Form: LIQUID
Manufacturer: Newton Laboratories, Inc.
Category: homeopathic | Type: HUMAN OTC DRUG LABEL
Date: 20240131

ACTIVE INGREDIENTS: ACONITUM NAPELLUS 15 [hp_X]/1 mL; BARIUM CARBONATE 15 [hp_X]/1 mL; BARIUM CHLORIDE DIHYDRATE 15 [hp_X]/1 mL; CAPSICUM 15 [hp_X]/1 mL; CAUSTICUM 15 [hp_X]/1 mL; DYSPHANIA AMBROSIOIDES 15 [hp_X]/1 mL; QUININE SULFATE 15 [hp_X]/1 mL; CINCHONA OFFICINALIS BARK 15 [hp_X]/1 mL; NITROGLYCERIN 15 [hp_X]/1 mL; GRAPHITE 15 [hp_X]/1 mL; GOLDENSEAL 15 [hp_X]/1 mL; POTASSIUM DICHROMATE 15 [hp_X]/1 mL; POTASSIUM CHLORIDE 15 [hp_X]/1 mL; LYCOPODIUM CLAVATUM SPORE 15 [hp_X]/1 mL; PHOSPHORUS 15 [hp_X]/1 mL; PULSATILLA VULGARIS 15 [hp_X]/1 mL; SALICYLIC ACID 15 [hp_X]/1 mL; TOBACCO LEAF 15 [hp_X]/1 mL; ALLYLTHIOUREA 15 [hp_X]/1 mL; VIOLA ODORATA 15 [hp_X]/1 mL
INACTIVE INGREDIENTS: ALCOHOL

Ear Ri-2588L

INDICATIONS & USAGE SECTION

Formulated for associated symptoms such as ringing, buzzing, echoing, pressure, pain, throbbing and sensitivity to noise.

DOSAGE & ADMINISTRATION SECTION

Directions: Ages 12 and up, take 6 drops by mouth (ages 0 to 11, give 3 drops) as needed or as directed by a health professional. Sensitive persons begin with 1 drop and gradually increase to full dose.

OTC - ACTIVE INGREDIENT SECTION

Equal parats of Hydrastis 6x, Aconitum nap. 15x, Baryta carb. 15x, Baryta mur. 15x, Capsicum 15x, Causticum 15x, Chenopodium anthelminticum 15x, Chininum sulphuricum 15x, Cinchona 15x, Glonoinum 15x, Graphites 15x, Hydrastis 15x, Kali bic. 15x, Kali mur.15x, Lycopodium 15x, Phosphorus 15x, Pulsatilla 15x, Salicylicum ac.15x, Tabacum 15x, Thiosinaminum 15x, Viola odorata 15x.

OTC - PURPOSE SECTION

Formulated for associated symptoms such as ringing, buzzing, echoing, pressure, pain, throbbing and sensitivity to noise.

INACTIVE INGREDIENT SECTION

Inactive Ingredients: USP Purified Water; USP Gluten-free, non-GMO, organic cane alcohol 20%

QUESTIONS SECTION

newtonlabs.net -Questions? 800.448.7256

Newton Laboratories, Inc. FDA Est # 1051203 - Conyers, GA 30013

WARNINGS SECTION

WARNINGS: Keep out of reach of children. Do not use if tamper-evident seal is broken or missing. If symptoms worsen or persist for more than a few days, consult a doctor. If pregnant or breast-feeding, ask a doctor before use.

OTC - PREGNANCY OR BREAST FEEDING SECTION

WARNINGS: If pregnant or breast-feeding, ask a doctor before use.

OTC - KEEP OUT OF REACH OF CHILDREN SECTION

WARNINGS: Keep out of reach of children.